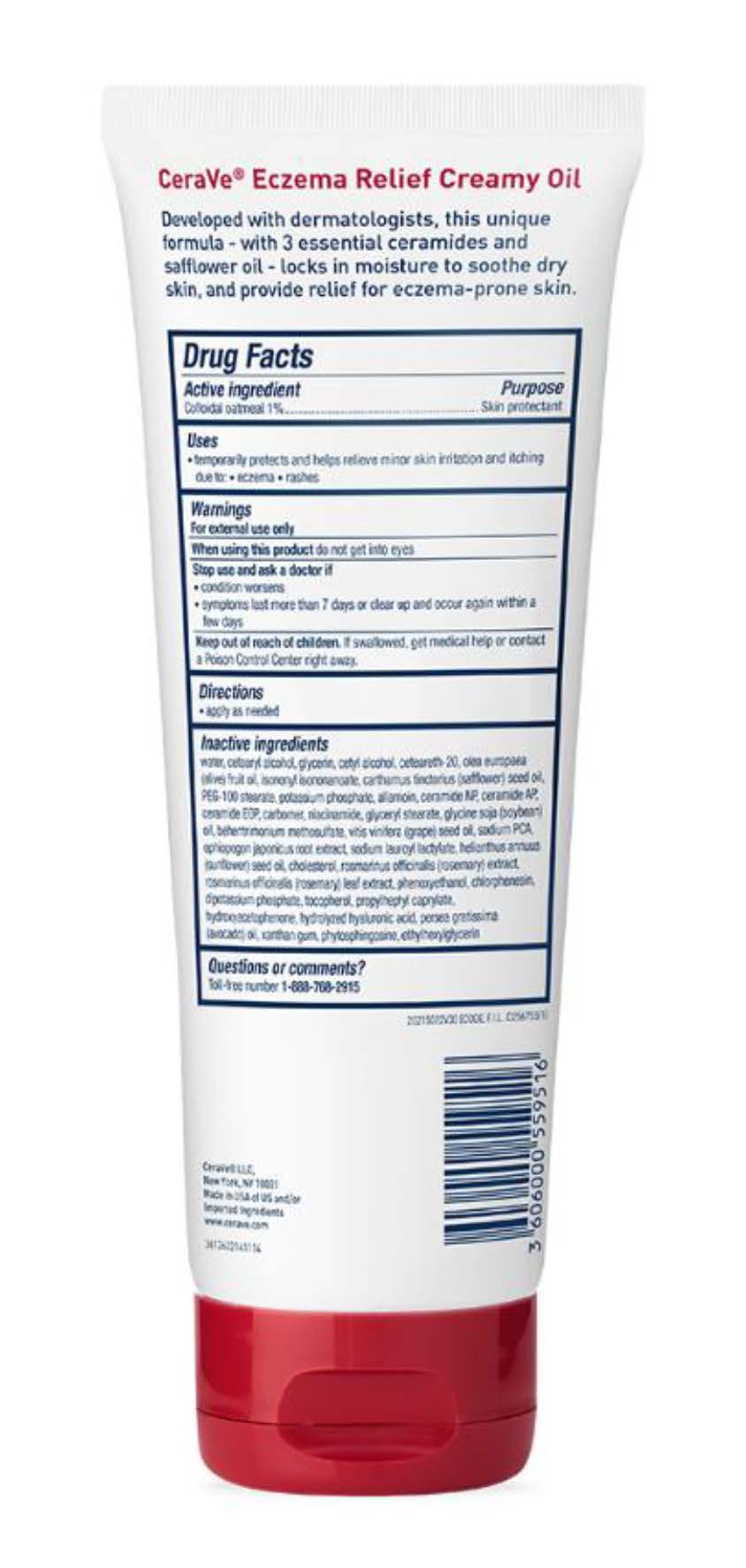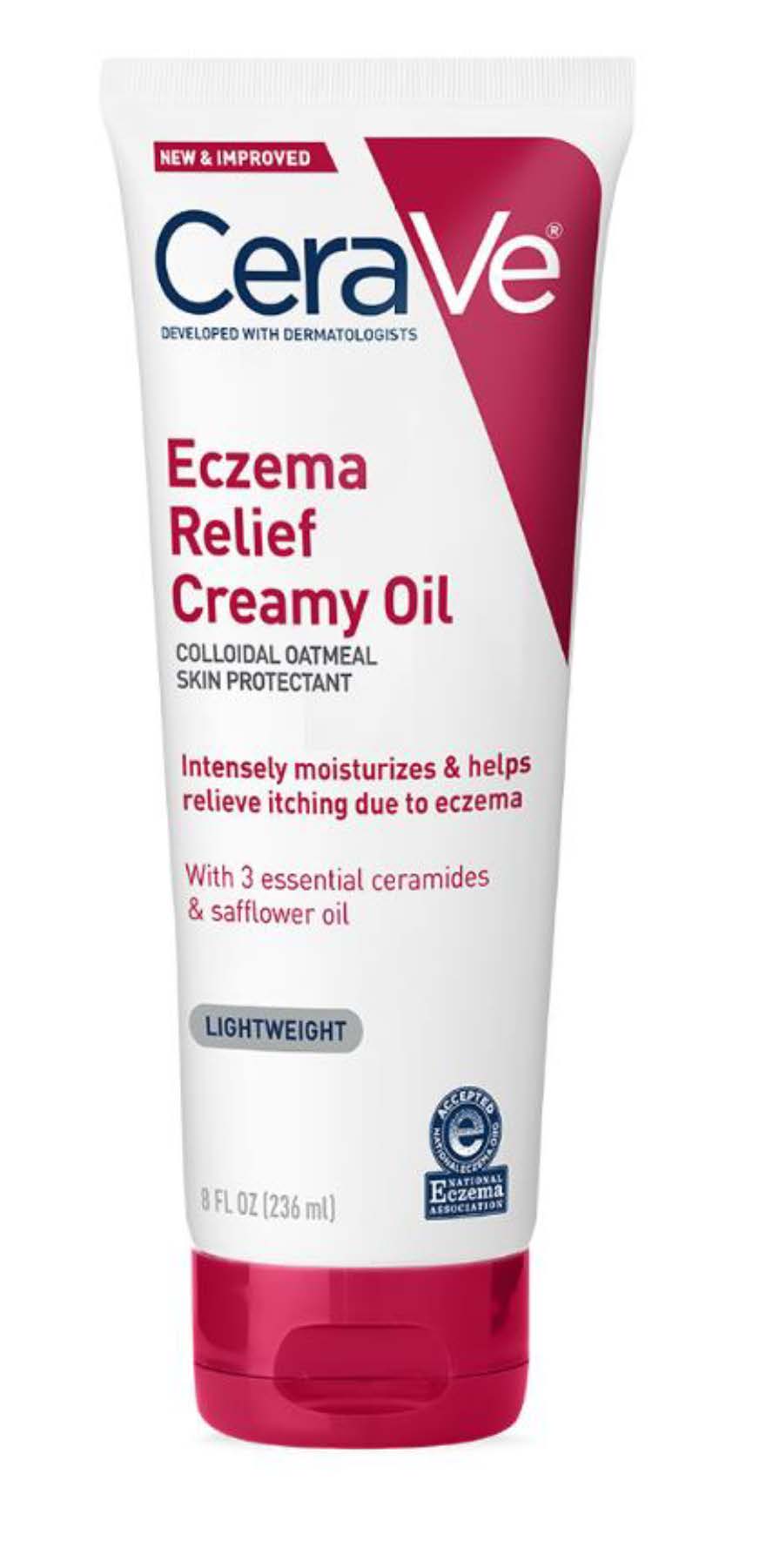 DRUG LABEL: CeraVe Developed with Dermatologists Eczema Relief Creamy
NDC: 49967-951 | Form: OIL
Manufacturer: L'Oreal USA Products Inc
Category: otc | Type: HUMAN OTC DRUG LABEL
Date: 20240101

ACTIVE INGREDIENTS: OATMEAL 10 mg/1 mL
INACTIVE INGREDIENTS: WATER; CETOSTEARYL ALCOHOL; GLYCERIN; CETYL ALCOHOL; POLYOXYL 20 CETOSTEARYL ETHER; OLIVE OIL; ISONONYL ISONONANOATE; SAFFLOWER OIL; PEG-100 STEARATE; MONOBASIC POTASSIUM PHOSPHATE; ALLANTOIN; CERAMIDE NP; CERAMIDE AP; CERAMIDE 1; CARBOMER HOMOPOLYMER, UNSPECIFIED TYPE; NIACINAMIDE; GLYCERYL MONOSTEARATE; SOYBEAN OIL; BEHENTRIMONIUM METHOSULFATE; GRAPE SEED OIL; SODIUM PYRROLIDONE CARBOXYLATE; OPHIOPOGON JAPONICUS ROOT; SODIUM LAUROYL LACTYLATE; SUNFLOWER OIL; CHOLESTEROL; ROSEMARY; PHENOXYETHANOL; CHLORPHENESIN; DIBASIC POTASSIUM PHOSPHATE; TOCOPHEROL; PROPYLHEPTYL CAPRYLATE; HYDROXYACETOPHENONE; HYALURONIC ACID; AVOCADO OIL; XANTHAN GUM; PHYTOSPHINGOSINE; ETHYLHEXYLGLYCERIN

Drug Facts

Active ingredient

Colloidal oatmeal 1%

Purpose

Skin protectant

Uses

- temporarily protects and helps relieve minor skin irritation and itching due to: •eczema •rashes

Warnings

For external use only

When using this product

do not get into eyes

Stop use and ask a doctor if

- condition worsens
- symptoms last more than 7 days or clear up and occur again within a few days

Keep out of reach of children.

If swallowed, get medical help or contact a Poison Control Center right away.

Directions

apply as needed

Inactive ingredients

water, cetearyl alcohol, glycerin, cetyl alcohol, ceteareth-20, olea europaea (olive) fruit oil, isononyl isononanoate, carthamus tinctorius (safflower) seed oil, PEG-100 stearate, potassium phosphate, allantoin, ceramide NP, ceramide AP, ceramide EOP, carbomer, niacinamide, glyceryl stearate. glycine soja (soybean) oil, behentrimonium methosulfate, vitis vinifera (grape) seed oil, sodium PCA, ophiopogon japonicus root extract, sodium lauroyl lactylate, helianthus annuus (sunflower) seed oil, cholesterol, rosmarinus officinalis (rosemary) extract, rosmarinus officinalis (rosemary) leaf extract, phenoxyethanol, chlorphenesin, dipotassium phosphate, tocopherol, propylheptyl caprylate, hydroxyacetophenone, hydrolyzed hyaluronic acid, persea gratissima (avocado) oil, xanthan gum, phytosphingosine, ethylhexylglycerin

Questions or comments?

Toll-free number 1-888-768-2915